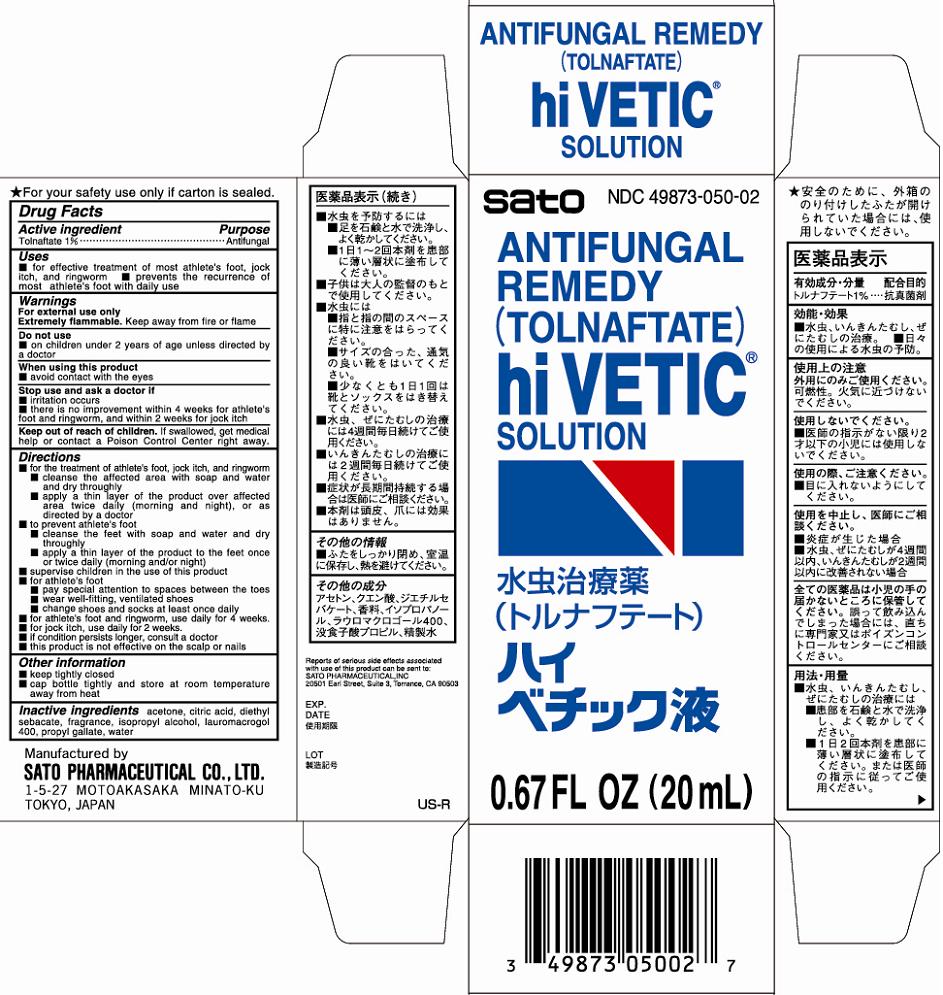 DRUG LABEL: Hi Vetic
NDC: 49873-050 | Form: SOLUTION
Manufacturer: Sato Pharmaceutical Co., Ltd.
Category: otc | Type: HUMAN OTC DRUG LABEL
Date: 20231201

ACTIVE INGREDIENTS: TOLNAFTATE 1 g/100 mL
INACTIVE INGREDIENTS: ACETONE; CITRIC ACID MONOHYDRATE; DIETHYL SEBACATE; ISOPROPYL ALCOHOL; POLIDOCANOL; PROPYL GALLATE; WATER

Hi Vetic Soln

Purpose Antifungal

Uses
■ for effective treatment of most athlete’s foot, jock itch, and ringworm ■prevents the recurrence of most athlete’s foot with daily use

Do not use
■on children under 2 years of age unless directed by a doctor

Warnings
For external use only
Extremely flammable. Keep away from fire or flame

When using this product
■avoid contact with the eyes

KEEP OUT OF REACH OF CHILDREN

Keep our of reach of children. If swallowed, get medical help or contact a Poison Control Center right away.

Stop use and ask a doctor if
■irritation occurs
■there is no improvement within 4 weeks for athlete’s foot and ringworm, and within 2 weeks for jock itch

Directions
■for the tratment of athlete’s foot, jock itch, and ringworm
■cleanse the affected area with soap and water and dry throughly
■apply a thin layer of the product over affected area twice daily (morning and night), or as directed by a doctor
■to prevent athlete’s foot
■cleanse the feet with soap and water and dry throughly
■apply a thin layer of the product to the feet once or twice daily (morning and/or night)
■supervise children in the use of this product
■for athlete’s foot
■pay special attention to spaces between the toes
■wear well-fitting, ventilated shoes
■change shoes and socks at least once daily
■for athlete’s foot and ringworm, use daily for 4 weeks.
■for jock itch, use daily for 2 weeks.
■if condition persists longer, consult a doctor
■this product is not effective on the scalp or nails

Other information
■keep tightly closed
■cap bottle tightly and store at room temperature away from heat

INACTIVE INGREDIENT

Inactive ingredients acetone, citric acid, diethyl sebacate, fragrance, isopropyl alcohol, lauromacrogol 400, propyl gallate, water

Active ingredient
Tolnaftate 1%

PACKAGE LABEL

hiveticsolncart.jpg